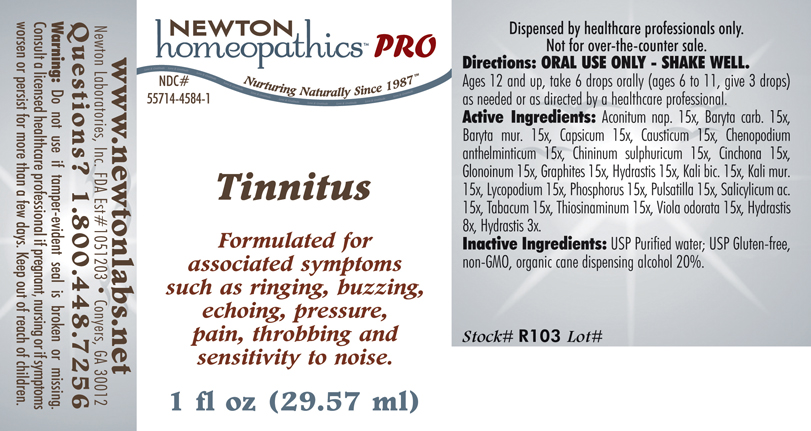 DRUG LABEL: Tinnitus 
NDC: 55714-4584 | Form: LIQUID
Manufacturer: Newton Laboratories, Inc.
Category: homeopathic | Type: HUMAN PRESCRIPTION DRUG LABEL
Date: 20110601

ACTIVE INGREDIENTS: Aconitum Napellus 15 [hp_X]/1 mL; Barium Carbonate 15 [hp_X]/1 mL; Barium Chloride Dihydrate 15 [hp_X]/1 mL; Capsicum 15 [hp_X]/1 mL; Causticum 15 [hp_X]/1 mL; Dysphania Ambrosioides 15 [hp_X]/1 mL; Quinine Sulfate 15 [hp_X]/1 mL; Cinchona Officinalis Bark 15 [hp_X]/1 mL; Nitroglycerin 15 [hp_X]/1 mL; Graphite 15 [hp_X]/1 mL; Goldenseal 15 [hp_X]/1 mL; Potassium Dichromate 15 [hp_X]/1 mL; Potassium Chloride 15 [hp_X]/1 mL; Lycopodium Clavatum Spore 15 [hp_X]/1 mL; Phosphorus 15 [hp_X]/1 mL; Pulsatilla Vulgaris 15 [hp_X]/1 mL; Salicylic Acid 15 [hp_X]/1 mL; Tobacco Leaf 15 [hp_X]/1 mL; Allylthiourea 15 [hp_X]/1 mL; Viola Odorata 15 [hp_X]/1 mL
INACTIVE INGREDIENTS: Alcohol

Tinnitus

INDICATIONS & USAGE SECTION

Tinnitus Formulated for associated symptoms such as ringing, buzzing, echoing, pressure, pain, throbbing and sensitivity to noise.

DOSAGE & ADMINISTRATION SECTION

Directions: ORAL USE ONLY - SHAKE WELL. Ages 12 and up, take 6 drops orally (ages 6 to 11, give 3 drops) as needed or as directed by a healthcare professional.

ACTIVE INGREDIENT SECTION

Aconitum nap. 15x, Baryta carb. 15x, Baryta mur. 15x, Capsicum 15x, Causticum 15x, Chenopodium anthelminticum 15x, Chininum sulphuricum 15x, Cinchona 15x, Glonoinum 15x, Graphites 15x, Hydrastis 15x, Kali bic. 15x, Kali mur.15x, Lycopodium 15x, Phosphorus 15x, Pulsatilla 15x, Salicylicum ac.15x, Tabacum 15x, Thiosinaminum 15x, Viola odorata 15x, Hydrastis 8x, Hydrastis 3x.

PURPOSE SECTION

Formulated for associated symptoms such as ringing, buzzing, echoing, pressure, pain, throbbing and sensitivity to noise.

INACTIVE INGREDIENT SECTION

Inactive Ingredients: USP Purified Water; USP Gluten-free, non-GMO, organic cane dispensing alcohol 20%.

QUESTIONS? SECTION

www.newtonlabs.net Newton Laboratories, Inc. FDA Est # 1051203 - Conyers, GA 30012
Questions? 1.800.448.7256

WARNINGS SECTION

Warning: Do not use if tamper - evident seal is broken or missing. Consult a licensed healthcare professional if pregnant, nursing or if symptoms worsen or persist for more than a few days. Keep out of reach of children.

PREGNANCY OR BREAST FEEDING SECTION

Consult a licensed healthcare professional if pregnant, nursing or if symptoms worsen or persist for more than a few days.

KEEP OUT OF REACH OF CHILDREN SECTION

Keep out of reach of children